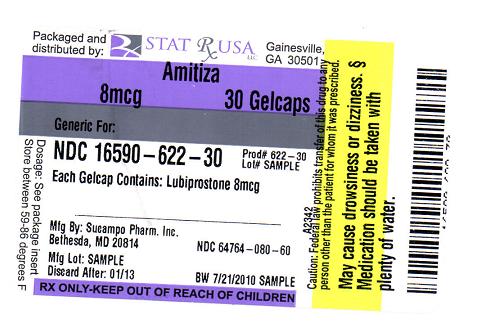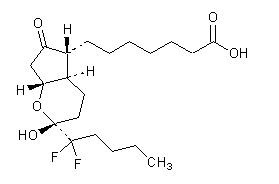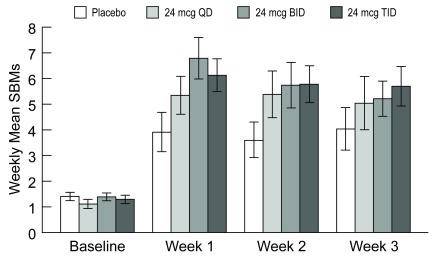 DRUG LABEL: AMITIZA
NDC: 16590-622 | Form: CAPSULE, GELATIN COATED
Manufacturer: STAT RX USA LLC
Category: prescription | Type: HUMAN PRESCRIPTION DRUG LABEL
Date: 20100721

ACTIVE INGREDIENTS: LUBIPROSTONE 8 ug/1 1
INACTIVE INGREDIENTS: MEDIUM-CHAIN TRIGLYCERIDES; GELATIN; SORBITOL; FERRIC OXIDE RED; TITANIUM DIOXIDE; WATER

HIGHLIGHTS OF PRESCRIBING INFORMATION

These highlights do not include all the information needed to use AMITIZA safely and effectively. See full prescribing information for AMITIZA.
AMITIZA (lubiprostone) capsule, gelatin coated for oral use
Initial U.S. Approval: 2006

1 INDICATIONS AND USAGE

Amitiza is a chloride channel activator indicated for:

- Treatment of chronic idiopathic constipation in adults (1.1)
- Treatment of irritable bowel syndrome with constipation in women ≥ 18 years old (1.2)

2 DOSAGE AND ADMINISTRATION

Chronic idiopathic constipation

- 24 mcg taken twice daily orally with food and water (2.1)

Irritable bowel syndrome with constipation

- 8 mcg taken twice daily orally with food and water (2.2)

3 DOSAGE FORMS AND STRENGTHS

- Gelatin capsules: 8 mcg and 24 mcg (3)

4 CONTRAINDICATIONS

- Patients with known or suspected mechanical gastrointestinal obstruction should not receive Amitiza (4)

5 WARNINGS AND PRECAUTIONS

- Women who could become pregnant should have a negative pregnancy test prior to beginning therapy and should be capable of complying with effective contraceptive measures (8.1)
- Use during pregnancy only if the potential benefit justifies the potential risk to the fetus (5.1)
- Patients may experience nausea; concomitant administration of food may reduce this symptom (5.2)
- Do not prescribe for patients that have severe diarrhea (5.3)
- Patients taking Amitiza may experience dyspnea within an hour of first dose. This symptom generally resolves within 3 hours, but may recur with repeat dosing (5.4)
- Evaluate patients with symptoms suggestive of mechanical gastrointestinal obstruction prior to initiating treatment with Amitiza (5.5)

6 ADVERSE REACTIONS

- Most common adverse reactions (incidence > 4%) in chronic idiopathic constipation are nausea, diarrhea, headache, abdominal pain, abdominal distension, and flatulence (6.1)
- Most common adverse reactions (incidence > 4%) in irritable bowel syndrome with constipation are nausea, diarrhea, and abdominal pain (6.1)

To report SUSPECTED ADVERSE REACTIONS, contact Takeda Pharmaceuticals North America, Inc., at 1-877-825-3327 or FDA at 1-800-FDA-1088 or www.fda.gov/medwatch

FULL PRESCRIBING INFORMATION

1 INDICATIONS AND USAGE

1.1 Chronic Idiopathic Constipation

Amitiza® is indicated for the treatment of chronic idiopathic constipation in adults.

1.2 Irritable Bowel Syndrome with Constipation

Amitiza is indicated for the treatment of irritable bowel syndrome with constipation (IBS-C) in women ≥ 18 years old.

2 DOSAGE AND ADMINISTRATION

Amitiza should be taken twice daily orally with food and water. Physicians and patients should periodically assess the need for continued therapy.

2.1 Chronic Idiopathic Constipation

24 mcg twice daily orally with food and water.

2.2 Irritable Bowel Syndrome with Constipation

8 mcg twice daily orally with food and water.

3 DOSAGE FORMS AND STRENGTHS

Amitiza is available as an oval, gelatin capsule containing 8 mcg or 24 mcg of lubiprostone.

- 8-mcg capsules are pink and are printed with "SPI" on one side
- 24-mcg capsules are orange and are printed with "SPI" on one side

4 CONTRAINDICATIONS

Amitiza is contraindicated in patients with known or suspected mechanical gastrointestinal obstruction.

5 WARNINGS AND PRECAUTIONS

5.1 Pregnancy

The safety of Amitiza in pregnancy has not been evaluated in humans. In guinea pigs, lubiprostone has been shown to have the potential to cause fetal loss. Amitiza should be used during pregnancy only if the potential benefit justifies the potential risk to the fetus. Women who could become pregnant should have a negative pregnancy test prior to beginning therapy with Amitiza and should be capable of complying with effective contraceptive measures. See Use in Specific Populations (8.1).

5.2 Nausea

Patients taking Amitiza may experience nausea. If this occurs, concomitant administration of food with Amitiza may reduce symptoms of nausea. See Adverse Reactions (6.1).

5.3 Diarrhea

Amitiza should not be prescribed to patients that have severe diarrhea. Patients should be aware of the possible occurrence of diarrhea during treatment. Patients should be instructed to inform their physician if severe diarrhea occurs. See Adverse Reactions (6.1).

5.4 Dyspnea

In clinical trials conducted to study Amitiza in treatment of chronic idiopathic constipation and IBS-C there were reports of dyspnea. This was reported at 2.5% of the treated chronic idiopathic constipation population and at 0.4% in the treated IBS-C population. Although not classified as serious adverse events, some patients discontinued treatment on study because of this event. There have been postmarketing reports of dyspnea when using Amitiza 24 mcg. Most have not been characterized as serious adverse events, but some patients have discontinued therapy because of dyspnea. These events have usually been described as a sensation of chest tightness and difficulty taking in a breath, and generally have an acute onset within 30–60 minutes after taking the first dose. They generally resolve within a few hours after taking the dose, but recurrence has been frequently reported with subsequent doses.

5.5 Bowel Obstruction

In patients with symptoms suggestive of mechanical gastrointestinal obstruction, the treating physician should perform a thorough evaluation to confirm the absence of such an obstruction prior to initiating therapy with Amitiza.

6 ADVERSE REACTIONS

6.1 Clinical Studies Experience

Because clinical studies are conducted under widely varying conditions, adverse reaction rates observed in the clinical studies of a drug cannot be directly compared to rates in the clinical studies of another drug and may not reflect the rates observed in practice.

Chronic Idiopathic Constipation

Adverse reactions in dose-finding, efficacy, and long-term clinical studies: The data described below reflect exposure to Amitiza in 1175 patients with chronic idiopathic constipation (29 at 24 mcg once daily, 1113 at 24 mcg twice daily, and 33 at 24 mcg three times daily) over 3- or 4-week, 6-month, and 12-month treatment periods; and from 316 patients receiving placebo over short-term exposure (≤ 4 weeks). The total population (N = 1491) had a mean age of 49.7 (range 19–86) years; was 87.1% female; 84.8% Caucasian, 8.5% African American, 5.0% Hispanic, 0.9% Asian; and 15.5% elderly (≥ 65 years of age). Table 1 presents data for the adverse reactions that occurred in at least 1% of patients who received Amitiza 24 mcg twice daily and that occurred more frequently with study drug than placebo. In addition, corresponding adverse reaction incidences in patients receiving Amitiza 24 mcg once daily is shown.

Table 1: Percent of Patients with Adverse Reactions (Chronic Idiopathic Constipation)
System/Adverse Reaction^1 | Placebo N = 316 % | Amitiza 24 mcg Once Daily N = 29 % | Amitiza 24 mcg Twice Daily N = 1113 %
Gastrointestinal disorders
Nausea | 3 | 17 | 29
Diarrhea | < 1 | 7 | 12
Abdominal pain | 3 | 3 | 8
Abdominal distension | 2 | - | 6
Flatulence | 2 | 3 | 6
Vomiting | - | - | 3
Loose stools | - | - | 3
Abdominal discomfort^2 | < 1 | 3 | 2
Dyspepsia | < 1 | - | 2
Dry mouth | < 1 | - | 1
Stomach discomfort | < 1 | - | 1
Nervous system disorders
Headache | 5 | 3 | 11
Dizziness | < 1 | 3 | 3
General disorders and site administration conditions
Edema | < 1 | - | 3
Fatigue | < 1 | - | 2
Chest discomfort/pain | - | 3 | 2
Respiratory, thoracic, and mediastinal disorders
Dyspnea | - | 3 | 2
^1Includes only those events associated with treatment (possibly, probably, or definitely related, as assessed by the investigator).
^2This term combines "abdominal tenderness," "abdominal rigidity," "gastrointestinal discomfort," and "abdominal discomfort."

Nausea: Approximately 29% of patients who received Amitiza 24 mcg twice daily experienced an adverse reaction of nausea; 4% of patients had severe nausea while 9% of patients discontinued treatment due to nausea. The rate of nausea associated with Amitiza (any dosage) was substantially lower among male (7%) and elderly patients (18%). Further analysis of the safety data revealed that long-term exposure to Amitiza does not appear to place patients at an elevated risk for experiencing nausea. The incidence of nausea increased in a dose-dependent manner with the lowest overall incidence for nausea reported at the 24 mcg once daily dosage (17%). In open-labeled, long-term studies, patients were allowed to adjust the dosage of Amitiza down to 24 mcg once daily from 24 mcg twice daily if experiencing nausea. Nausea decreased when Amitiza was administered with food. No patients in the clinical studies were hospitalized due to nausea.

Diarrhea: Approximately 12% of patients who received Amitiza 24 mcg twice daily experienced an adverse reaction of diarrhea; 2% of patients had severe diarrhea while 2% of patients discontinued treatment due to diarrhea.

Electrolytes: No serious adverse reactions of electrolyte imbalance were reported in clinical studies, and no clinically significant changes were seen in serum electrolyte levels in patients receiving Amitiza.

Less common adverse reactions: The following adverse reactions (assessed by investigator as probably or definitely related to treatment) occurred in less than 1% of patients receiving Amitiza 24 mcg twice daily in clinical studies, occurred in at least two patients, and occurred more frequently in patients receiving study drug than those receiving placebo: fecal incontinence, muscle cramp, defecation urgency, frequent bowel movements, hyperhidrosis, pharyngolaryngeal pain, intestinal functional disorder, anxiety, cold sweat, constipation, cough, dysgeusia, eructation, influenza, joint swelling, myalgia, pain, syncope, tremor, decreased appetite.

Irritable Bowel Syndrome with Constipation

Adverse reactions in dose-finding, efficacy, and long-term clinical studies: The data described below reflect exposure to Amitiza 8 mcg twice daily in 1011 patients with IBS-C for up to 12 months and from 435 patients receiving placebo twice daily for up to 16 weeks. The total population (N = 1267) had a mean age of 46.5 (range 18–85) years; was 91.6% female; 77.5% Caucasian, 12.9% African American, 8.6% Hispanic, 0.4% Asian; and 8.0% elderly (≥ 65 years of age). Table 2 presents data for the adverse reactions that occurred in at least 1% of patients who received Amitiza 8 mcg twice daily and that occurred more frequently with study drug than placebo.

Table 2: Percent of Patients with Adverse Reactions (IBS-C Studies)
System/Adverse Reaction^1 | Placebo N = 435 % | Amitiza 8 mcg Twice Daily N = 1011 %
Gastrointestinal disorders
Nausea | 4 | 8
Diarrhea | 4 | 7
Abdominal pain | 5 | 5
Abdominal distension | 2 | 3
^1Includes only those events associated with treatment (possibly or probably related, as assessed by the investigator).

Less common adverse reactions: The following adverse reactions (assessed by investigator as probably related to treatment) occurred in less than 1% of patients receiving Amitiza 8 mcg twice daily in clinical studies, occurred in at least two patients, and occurred more frequently in patients receiving study drug than those receiving placebo: dyspepsia, loose stools, vomiting, fatigue, dry mouth, edema, increased alanine aminotransferase, increased aspartate aminotransferase, constipation, eructation, gastroesophageal reflux disease, dyspnea, erythema, gastritis, increased weight, palpitations, urinary tract infection, anorexia, anxiety, depression, fecal incontinence, fibromyalgia, hard feces, lethargy, rectal hemorrhage, pollakiuria.

One open-labeled, long-term clinical study was conducted in patients with IBS-C receiving Amitiza 8 mcg twice daily. This study comprised 476 intent-to-treat patients (mean age 47.5 [range 21–82] years; 93.5% female; 79.2% Caucasian, 11.6% African American, 8.6% Hispanic, 0.2% Asian; 7.8% ≥ 65 years of age) who were treated for an additional 36 weeks following an initial 12–16-week, double-blinded treatment period. The adverse reactions that were reported during this study were similar to those observed in the two double-blinded, controlled studies.

6.2 Postmarketing Experience

The following adverse reactions have been identified during post-approval use of Amitiza 24 mcg for the treatment of chronic idiopathic constipation. Because these reactions are reported voluntarily from a population of uncertain size, it is not always possible to reliably estimate their frequency or establish a causal relationship to drug exposure.

Voluntary reports of adverse reactions occurring with the use of Amitiza include the following: syncope, allergic-type reactions (including rash, swelling, and throat tightness), malaise, increased heart rate, muscle cramps or muscle spasms, rash, and asthenia.

7 DRUG INTERACTIONS

Based upon the results of in vitro human microsome studies, there is low likelihood of drug–drug interactions. In vitro studies using human liver microsomes indicate that cytochrome P450 isoenzymes are not involved in the metabolism of lubiprostone. Further in vitro studies indicate microsomal carbonyl reductase may be involved in the extensive biotransformation of lubiprostone to the metabolite M3 (See Pharmacokinetics [12.3].). Additionally, in vitro studies in human liver microsomes demonstrate that lubiprostone does not inhibit cytochrome P450 isoforms 3A4, 2D6, 1A2, 2A6, 2B6, 2C9, 2C19, or 2E1, and in vitro studies of primary cultures of human hepatocytes show no induction of cytochrome P450 isoforms 1A2, 2B6, 2C9, and 3A4 by lubiprostone. No drug–drug interaction studies have been performed. Based on the available information, no protein binding–mediated drug interactions of clinical significance are anticipated.

8 USE IN SPECIFIC POPULATIONS

8.1 Pregnancy

TERATOGENIC EFFECTS

Teratogenic effects: Pregnancy Category C. [See Warnings and Precautions (5.1).]

Teratology studies with lubiprostone have been conducted in rats at oral doses up to 2000 mcg/kg/day (approximately 332 times the recommended human dose, based on body surface area), and in rabbits at oral doses of up to 100 mcg/kg/day (approximately 33 times the recommended human dose, based on body surface area). Lubiprostone was not teratogenic in rats or rabbits. In guinea pigs, lubiprostone caused fetal loss at repeated doses of 10 and 25 mcg/kg/day (approximately 2 and 6 times the highest recommended human dose, respectively, based on body surface area) administered on days 40 to 53 of gestation.

There are no adequate and well-controlled studies in pregnant women. However, during clinical testing of Amitiza, six women became pregnant. Per protocol, Amitiza was discontinued upon pregnancy detection. Four of the six women delivered healthy babies. The fifth woman was monitored for 1 month following discontinuation of study drug, at which time the pregnancy was progressing as expected; the patient was subsequently lost to follow-up. The sixth pregnancy was electively terminated.

Amitiza should be used during pregnancy only if the potential benefit justifies the potential risk to the fetus. If a woman is or becomes pregnant while taking the drug, the patient should be apprised of the potential hazard to the fetus.

8.3 Nursing Mothers

It is not known whether lubiprostone is excreted in human milk. Because many drugs are excreted in human milk and because of the potential for serious adverse reactions in nursing infants from lubiprostone, a decision should be made whether to discontinue nursing or to discontinue the drug, taking into account the importance of the drug to the mother.

8.4 Pediatric Use

Safety and effectiveness in pediatric patients have not been studied.

8.5 Geriatric Use

Chronic Idiopathic Constipation

The efficacy of Amitiza in the elderly (≥ 65 years of age) subpopulation was consistent with the efficacy in the overall study population. Of the total number of constipated patients treated in the dose-finding, efficacy, and long-term studies of Amitiza, 15.5% were ≥ 65 years of age, and 4.2% were ≥ 75 years of age. Elderly patients taking Amitiza (any dosage) experienced a lower incidence rate of associated nausea compared to the overall study population taking Amitiza (18% vs. 29%, respectively).

Irritable Bowel Syndrome with Constipation

The safety profile of Amitiza in the elderly (≥ 65 years of age) subpopulation (8.0% were ≥ 65 years of age and 1.8% were ≥ 75 years of age) was consistent with the safety profile in the overall study population. Clinical studies of Amitiza did not include sufficient numbers of patients aged 65 years and over to determine whether they respond differently from younger patients.

8.6 Renal Impairment

Amitiza has not been studied in patients who have renal impairment.

8.7 Hepatic Impairment

Amitiza has not been studied in patients who have hepatic impairment.

10 OVERDOSAGE

There have been two confirmed reports of overdosage with Amitiza. The first report involved a 3-year-old child who accidentally ingested 7 or 8 capsules of 24 mcg of Amitiza and fully recovered. The second report was a study patient who self-administered a total of 96 mcg of Amitiza per day for 8 days. The patient experienced no adverse reactions during this time. Additionally, in a Phase 1 cardiac repolarization study, 38 of 51 patients given a single oral dose of 144 mcg of Amitiza (6 times the highest recommended dose) experienced an adverse event that was at least possibly related to the study drug. Adverse reactions that occurred in at least 1% of these patients included the following: nausea (45%), diarrhea (35%), vomiting (27%), dizziness (14%), headache (12%), abdominal pain (8%), flushing/hot flash (8%), retching (8%), dyspnea (4%), pallor (4%), stomach discomfort (4%), anorexia (2%), asthenia (2%), chest discomfort (2%), dry mouth (2%), hyperhidrosis (2%), and syncope (2%).

11 DESCRIPTION

Amitiza (lubiprostone) is chemically designated as (–)-7-[(2R,4aR,5R,7aR)-2-(1,1-difluoropentyl)-2-hydroxy-6-oxooctahydrocyclopenta[b]pyran-5-yl]heptanoic acid. The molecular formula of lubiprostone is C20H32F2O5 with a molecular weight of 390.46 and a chemical structure as follows:

Lubiprostone drug substance occurs as white, odorless crystals or crystalline powder, is very soluble in ether and ethanol, and is practically insoluble in hexane and water. Amitiza is available as an imprinted, oval, soft gelatin capsule in two strengths. Pink capsules contain 8 mcg of lubiprostone and the following inactive ingredients: medium-chain triglycerides, gelatin, sorbitol, ferric oxide, titanium dioxide, and purified water. Orange capsules contain 24 mcg of lubiprostone and the following inactive ingredients: medium-chain triglycerides, gelatin, sorbitol, FD&C Red #40, D&C Yellow #10, and purified water.

12 CLINICAL PHARMACOLOGY

12.1 Mechanism of Action

Lubiprostone is a locally acting chloride channel activator that enhances a chloride-rich intestinal fluid secretion without altering sodium and potassium concentrations in the serum. Lubiprostone acts by specifically activating ClC-2, which is a normal constituent of the apical membrane of the human intestine, in a protein kinase A–independent fashion. By increasing intestinal fluid secretion, lubiprostone increases motility in the intestine, thereby facilitating the passage of stool and alleviating symptoms associated with chronic idiopathic constipation. Patch clamp cell studies in human cell lines have indicated that the majority of the beneficial biological activity of lubiprostone and its metabolites is observed only on the apical (luminal) portion of the gastrointestinal epithelium. Additionally, activation of ClC-2 by lubiprostone has been shown to stimulate recovery of mucosal barrier function via the restoration of tight junction protein complexes in ex vivo studies of ischemic porcine intestine.

12.2 Pharmacodynamics

Although the pharmacologic effects of lubiprostone in humans have not been fully evaluated, animal studies have shown that oral administration of lubiprostone increases chloride ion transport into the intestinal lumen, enhances fluid secretion into the bowels, and improves fecal transit.

12.3 Pharmacokinetics

Lubiprostone has low systemic availability following oral administration and concentrations of lubiprostone in plasma are below the level of quantitation (10 pg/mL). Therefore, standard pharmacokinetic parameters such as area under the curve (AUC), maximum concentration (Cmax), and half-life (t½) cannot be reliably calculated. However, the pharmacokinetic parameters of M3 (only measurable active metabolite of lubiprostone) have been characterized. Gender has no effect on the pharmacokinetics of M3 following the oral administration of lubiprostone.

Absorption

Concentrations of lubiprostone in plasma are below the level of quantitation (10 pg/mL) because lubiprostone has a low systemic availability following oral administration. Peak plasma levels of M3, after a single oral dose with 24 mcg of lubiprostone, occurred at approximately 1.10 hours. The Cmax was 41.5 pg/mL and the mean AUC0–t was 57.1 pg∙hr/mL. The AUC0–t of M3 increases dose proportionally after single 24-mcg and 144-mcg doses of lubiprostone.

Distribution

In vitro protein binding studies indicate lubiprostone is approximately 94% bound to human plasma proteins. Studies in rats given radiolabeled lubiprostone indicate minimal distribution beyond the gastrointestinal tissues. Concentrations of radiolabeled lubiprostone at 48 hours post-administration were minimal in all tissues of the rats.

Metabolism

The results of both human and animal studies indicate that lubiprostone is rapidly and extensively metabolized by 15-position reduction, α-chain β-oxidation, and ω-chain ω-oxidation. These biotransformations are not mediated by the hepatic cytochrome P450 system but rather appear to be mediated by the ubiquitously expressed carbonyl reductase. M3, a metabolite of lubiprostone found in both humans and animals, is formed by the reduction of the carbonyl group at the 15-hydroxy moiety that consists of both α-hydroxy and β-hydroxy epimers. M3 makes up less than 10% of the dose of radiolabeled lubiprostone. Animal studies have shown that metabolism of lubiprostone rapidly occurs within the stomach and jejunum, most likely in the absence of any systemic absorption. This is presumed to be the case in humans as well.

Elimination

Lubiprostone could not be detected in plasma; however, M3 has a t½ ranging from 0.9 to 1.4 hours. After a single oral dose of 72 mcg of ^3H-labeled lubiprostone, 60% of total administered radioactivity was recovered in the urine within 24 hours and 30% of total administered radioactivity was recovered in the feces by 168 hours. Lubiprostone and M3 are only detected in trace amounts in human feces.

Food Effect

A study was conducted with a single 72-mcg dose of ^3H-labeled lubiprostone to evaluate the potential of a food effect on lubiprostone absorption, metabolism, and excretion. Pharmacokinetic parameters of total radioactivity demonstrated that Cmax decreased by 55% while AUC0–∞ was unchanged when lubiprostone was administered with a high-fat meal. The clinical relevance of the effect of food on the pharmacokinetics of lubiprostone is not clear. However, lubiprostone was administered with food and water in a majority of clinical trials.

13 NONCLINICAL TOXICOLOGY

13.1 Carcinogenesis, Mutagenesis, Impairment of Fertility

Carcinogenesis

Two 2-year oral (gavage) carcinogenicity studies (one in Crl:B6C3F1 mice and one in Sprague-Dawley rats) were conducted with lubiprostone. In the 2-year carcinogenicity study in mice, lubiprostone doses of 25, 75, 200, and 500 mcg/kg/day (approximately 2, 6, 17, and 42 times the highest recommended human dose, respectively, based on body surface area) were used. In the 2-year rat carcinogenicity study, lubiprostone doses of 20, 100, and 400 mcg/kg/day (approximately 3, 17, and 68 times the highest recommended human dose, respectively, based on body surface area) were used. In the mouse carcinogenicity study, there was no significant increase in any tumor incidences. There was a significant increase in the incidence of interstitial cell adenoma of the testes in male rats at the 400 mcg/kg/day dose. In female rats, treatment with lubiprostone produced hepatocellular adenoma at the 400 mcg/kg/day dose.

Mutagenesis

Lubiprostone was not genotoxic in the in vitro Ames reverse mutation assay, the in vitro mouse lymphoma (L5178Y TK +/–) forward mutation assay, the in vitro Chinese hamster lung (CHL/IU) chromosomal aberration assay, and the in vivo mouse bone marrow micronucleus assay.

Impairment of Fertility

Lubiprostone, at oral doses of up to 1000 mcg/kg/day, had no effect on the fertility and reproductive function of male and female rats. However, the number of implantation sites and live embryos were significantly reduced in rats at the 1000 mcg/kg/day dose as compared to control. The number of dead or resorbed embryos in the 1000 mcg/kg/day group was higher compared to the control group, but was not statistically significant. The 1000 mcg/kg/day dose in rats is approximately 166 times the highest recommended human dose of 48 mcg/day, based on body surface area.

14 CLINICAL STUDIES

14.1 Chronic Idiopathic Constipation

Dose-finding Study

A dose-finding, double-blinded, parallel-group, placebo-controlled, Phase 2 study was conducted in patients with chronic idiopathic constipation. Following a 2-week baseline/washout period, patients (N = 127) were randomized to receive placebo (n = 33), Amitiza 24 mcg/day (24 mcg once daily; n = 29), Amitiza 48 mcg/day (24 mcg twice daily; n = 32), or Amitiza 72 mcg/day (24 mcg three times daily; n = 33) for 3 weeks. Patients were chosen for participation based on their need for relief of constipation, which was defined as less than 3 spontaneous bowel movements (SBMs) per week. The primary efficacy variable was the daily average number of SBMs.

The study demonstrated that all patients who took Amitiza experienced a noticeable improvement in clinical response. Based on the efficacy analysis, there was no statistically significant improvement in the clinical response beyond a total daily dose of 24 mcg during treatment weeks 2 and 3 (Figure 1).

Figure 1: Weekly Mean (± Standard Error) Spontaneous Bowel Movements (Dose-finding Study)

Efficacy Studies

Two double-blinded, placebo-controlled studies of identical design were conducted in patients with chronic idiopathic constipation. Chronic idiopathic constipation was defined as, on average, less than 3 SBMs per week along with one or more of the following symptoms of constipation for at least 6 months prior to randomization: 1) very hard stools for at least a quarter of all bowel movements; 2) sensation of incomplete evacuation following at least a quarter of all bowel movements; and 3) straining with defecation at least a quarter of the time.

Following a 2-week baseline/washout period, a total of 479 patients (mean age 47.2 [range 20–81] years; 88.9% female; 80.8% Caucasian, 9.6% African American, 7.3% Hispanic, 1.5% Asian; 10.9% ≥ 65 years of age) were randomized and received Amitiza 24 mcg twice daily (48 mcg/day) or placebo twice daily for 4 weeks. The primary endpoint of the studies was SBM frequency. The studies demonstrated that patients treated with Amitiza had a higher frequency of SBMs during Week 1 than the placebo patients. In both studies, results similar to those in Week 1 were also observed in Weeks 2, 3, and 4 of therapy (Table 3).

Table 3: Spontaneous Bowel Movement Frequency Rates^1 (Efficacy Studies)
Trial | Study Arm | Baseline Mean ± SD Median | Week 1 Mean ± SD Median | Week 2 Mean ± SD Median | Week 3 Mean ± SD Median | Week 4 Mean ± SD Median | Week 1 Change from Baseline Mean ± SD Median | Week 4 Change from Baseline Mean ± SD Median
 | Placebo | 1.6 ± 1.3 1.5 | 3.5 ± 2.3 3.0 | 3.2 ± 2.5 3.0 | 2.8 ± 2.2 2.0 | 2.9 ± 2.4 2.3 | 1.9 ± 2.2 1.5 | 1.3 ± 2.5 1.0
Study 1
 | Amitiza 24 mcg Twice Daily | 1.4 ± 0.8 1.5 | 5.7 ± 4.4 5.0 | 5.1 ± 4.1 4.0 | 5.3 ± 4.9 5.0 | 5.3 ± 4.7 4.0 | 4.3 ± 4.3 3.5 | 3.9 ± 4.6 3.0
 | Placebo | 1.5 ± 0.8 1.5 | 4.0 ± 2.7 3.5 | 3.6 ± 2.7 3.0 | 3.4 ± 2.8 3.0 | 3.5 ± 2.9 3.0 | 2.5 ± 2.6 1.5 | 1.9 ± 2.7 1.5
Study 2
 | Amitiza 24 mcg Twice Daily | 1.3 ± 0.9 1.5 | 5.9 ± 4.0 5.0 | 5.0 ± 4.2 4.0 | 5.6 ± 4.6 5.0 | 5.4 ± 4.8 4.3 | 4.6 ± 4.1 3.8 | 4.1 ± 4.8 3.0
^1Frequency rates are calculated as 7 times (number of SBMs) / (number of days observed for that week).

In both studies, Amitiza demonstrated increases in the percentage of patients who experienced SBMs within the first 24 hours after administration when compared to placebo (56.7% vs. 36.9% in Study 1 and 62.9% vs. 31.9% in Study 2, respectively). Similarly, the time to first SBM was shorter for patients receiving Amitiza than for those receiving placebo.

Signs and symptoms related to constipation, including abdominal bloating, abdominal discomfort, stool consistency, and straining, as well as constipation severity ratings, were also improved with Amitiza versus placebo. The results were consistent in subpopulation analyses for gender, race, and elderly patients (≥ 65 years of age).

Following 4 weeks of treatment with Amitiza 24 mcg twice daily, withdrawal of Amitiza did not result in a rebound effect.

Long-term Studies

Three open-labeled, long-term clinical safety and efficacy studies were conducted in patients with chronic idiopathic constipation receiving Amitiza 24 mcg twice daily. These studies comprised 871 patients (mean age 51.0 [range 19–86] years; 86.1% female; 86.9% Caucasian, 7.3% African American, 4.5% Hispanic, 0.7% Asian; 18.4% ≥ 65 years of age) who were treated for 6–12 months (24–48 weeks). Patients provided regular assessments of abdominal bloating, abdominal discomfort, and constipation severity. These studies demonstrated that Amitiza decreased abdominal bloating, abdominal discomfort, and constipation severity over the 6–12-month treatment periods.

14.2 Irritable Bowel Syndrome with Constipation

Efficacy Studies

Two double-blinded, placebo-controlled studies of similar design were conducted in patients with IBS-C. IBS was defined as abdominal pain or discomfort occurring over at least 6 months with two or more of the following: 1) relieved with defecation; 2) onset associated with a change in stool frequency; and 3) onset associated with a change in stool form. Patients were sub-typed as having IBS-C if they also experienced two of three of the following: 1) < 3 spontaneous bowel movements per week, 2) > 25% hard stools, and 3) > 25% spontaneous bowel movements associated with straining.

Following a 4-week baseline/washout period, a total of 1154 patients (mean age 46.6 [range 18–85] years; 91.6% female; 77.4% Caucasian, 13.2% African American, 8.5% Hispanic, 0.4% Asian; 8.3% ≥ 65 years of age) were randomized and received Amitiza 8 mcg twice daily (16 mcg/day) or placebo twice daily for 12 weeks. The primary efficacy endpoint was assessed weekly utilizing the patient's response to a global symptom relief question based on a 7-point, balanced scale ("significantly worse" to "significantly relieved"): "How would you rate your relief of IBS symptoms (abdominal discomfort/pain, bowel habits, and other IBS symptoms) over the past week compared to how you felt before you entered the study?"

The primary efficacy analysis was a comparison of the proportion of "overall responders" in each arm. A patient was considered an "overall responder" if the criteria for being designated a "monthly responder" were met in at least 2 of the 3 months on study. A "monthly responder" was defined as a patient who had reported "significantly relieved" for at least 2 weeks of the month or at least "moderately relieved" in all 4 weeks of that month. During each monthly evaluation period, patients reporting "moderately worse" or "significantly worse" relief, an increase in rescue medication use, or those who discontinued due to lack of efficacy, were deemed non-responders.

The percentage of patients in Study 1 qualifying as an "overall responder" was 13.8% in the group receiving Amitiza 8 mcg twice daily compared to 7.8% of patients receiving placebo twice daily. In Study 2, 12.1% of patients in the Amitiza 8 mcg group were "overall responders" versus 5.7% of patients in the placebo group. In both studies, the treatment differences between the placebo and Amitiza groups were statistically significant.

Results in men: The two randomized, placebo-controlled, double-blinded studies comprised 97 (8.4%) male patients, which is insufficient to determine whether men with IBS-C respond differently to Amitiza from women.

Study 1 also assessed the rebound effect from the withdrawal of Amitiza. Following 12 weeks of treatment with Amitiza 8 mcg twice daily, withdrawal of Amitiza did not result in a rebound effect.

16 HOW SUPPLIED/STORAGE AND HANDLING

Amitiza is available as an oval, soft gelatin capsule containing 8 mcg or 24 mcg of lubiprostone with "SPI" printed on one side. Amitiza is available as follows:

8-mcg pink capsule

- Bottles of 60 (NDC 64764-080-60)

24-mcg orange capsule

- Bottles of 60 (NDC 64764-240-60)
- Bottles of 100 (NDC 64764-240-10)

Store at 25°C (77°F); excursions permitted to 15°–30°C (59°–86°F).

PROTECT FROM EXTREME TEMPERATURES.

17 PATIENT COUNSELING INFORMATION

17.1 Dosing Instructions

Amitiza should be taken twice daily with food and water to reduce potential symptoms of nausea. The capsule should be taken once in the morning and once in the evening daily as prescribed. The capsule should be swallowed whole and should not be broken apart or chewed. Physicians and patients should periodically assess the need for continued therapy.

Patients on treatment who experience severe nausea, diarrhea, or dyspnea should inform their physician. Patients taking Amitiza may experience dyspnea within an hour of the first dose. This symptom generally resolves within 3 hours, but may recur with repeat dosing.

Chronic Idiopathic Constipation

Patients should take a single 24 mcg capsule of Amitiza twice daily with food and water.

Irritable Bowel Syndrome with Constipation

Patients should take a single 8 mcg capsule of Amitiza twice daily with food and water.

Marketed by:

Sucampo Pharma Americas, Inc.
Bethesda, MD 20814

and

Takeda Pharmaceuticals America, Inc.
Deerfield, IL 60015

Amitiza® is a registered trademark of Sucampo Pharmaceuticals, Inc.

AMITIZA 8MCG LABEL IMAGE